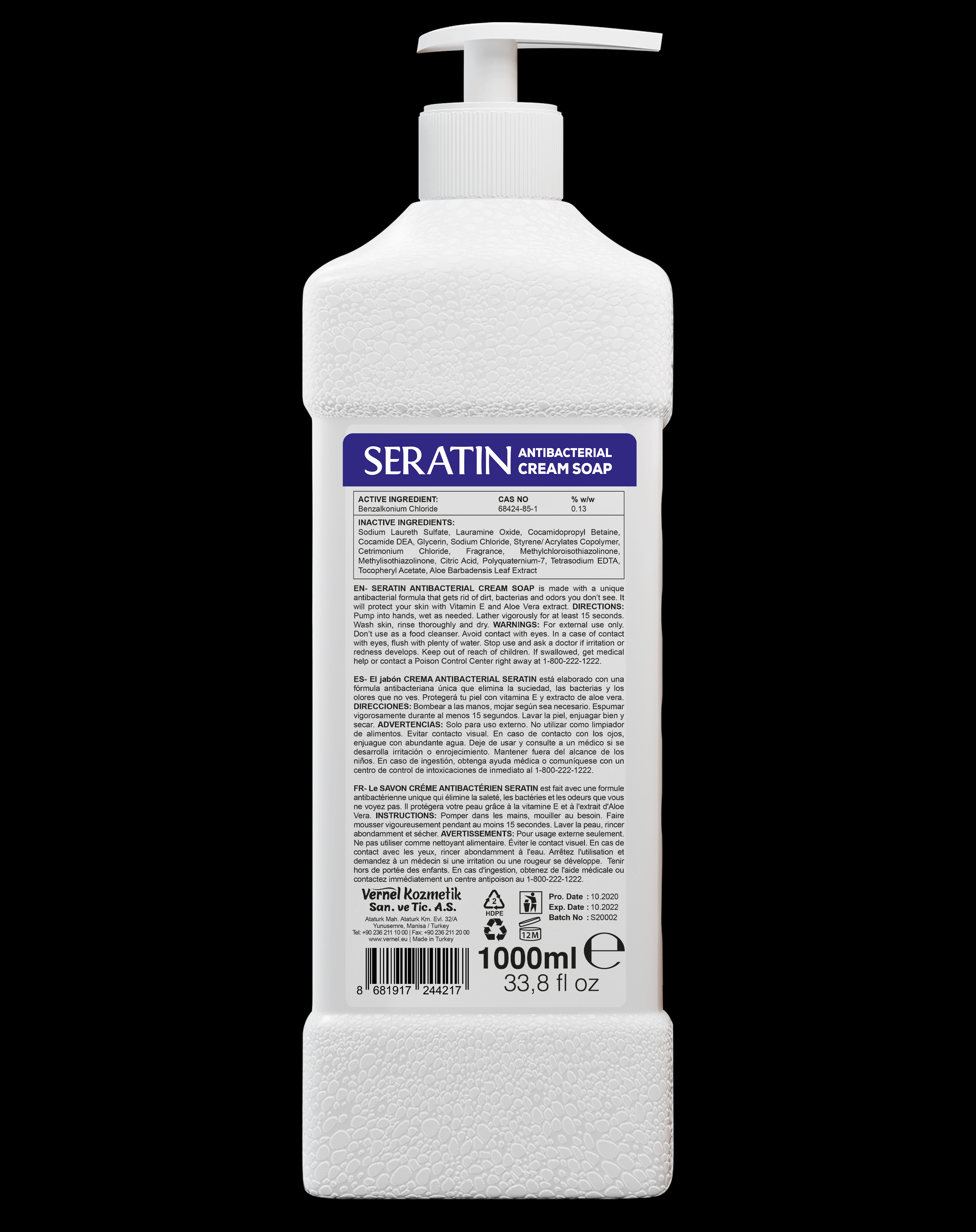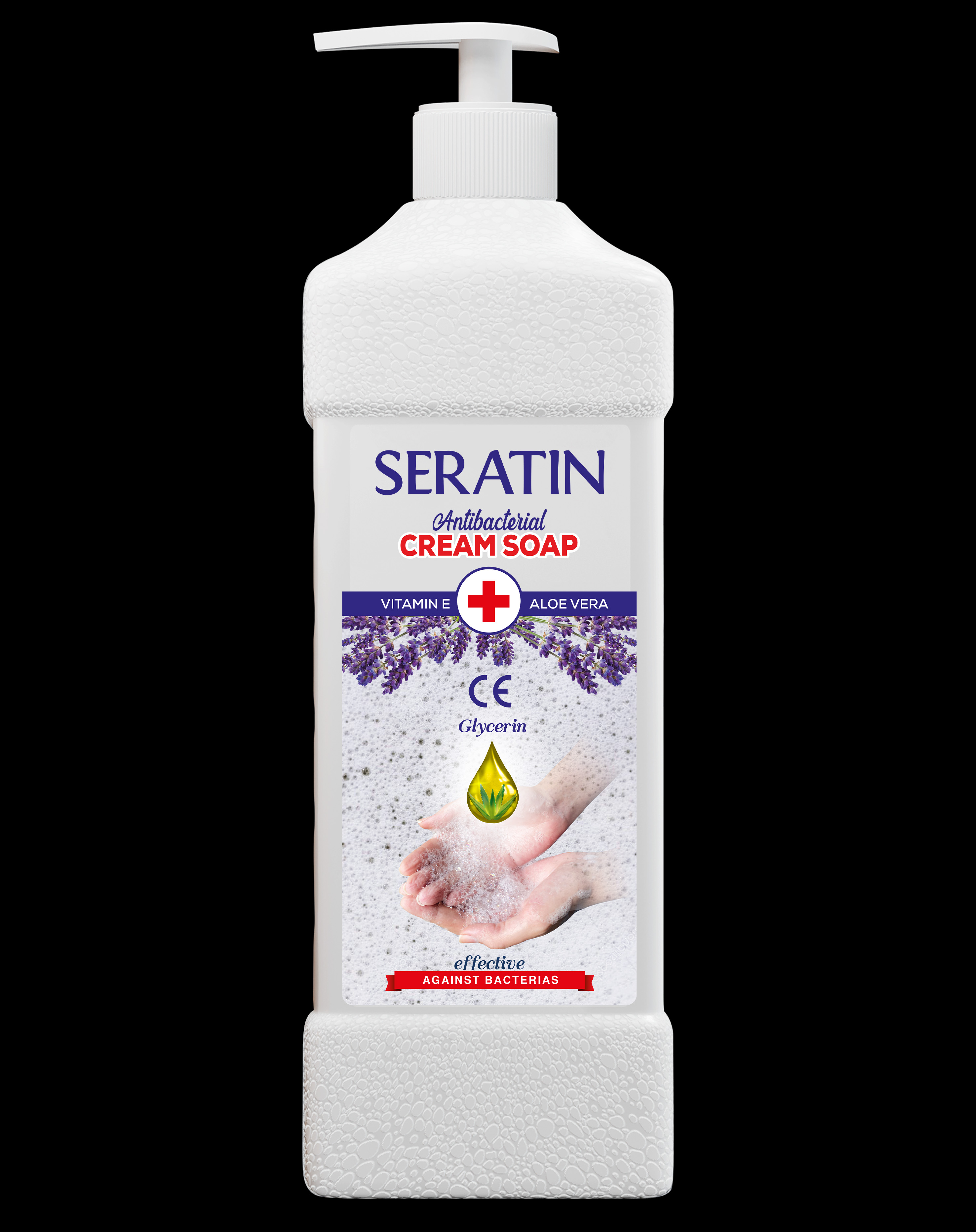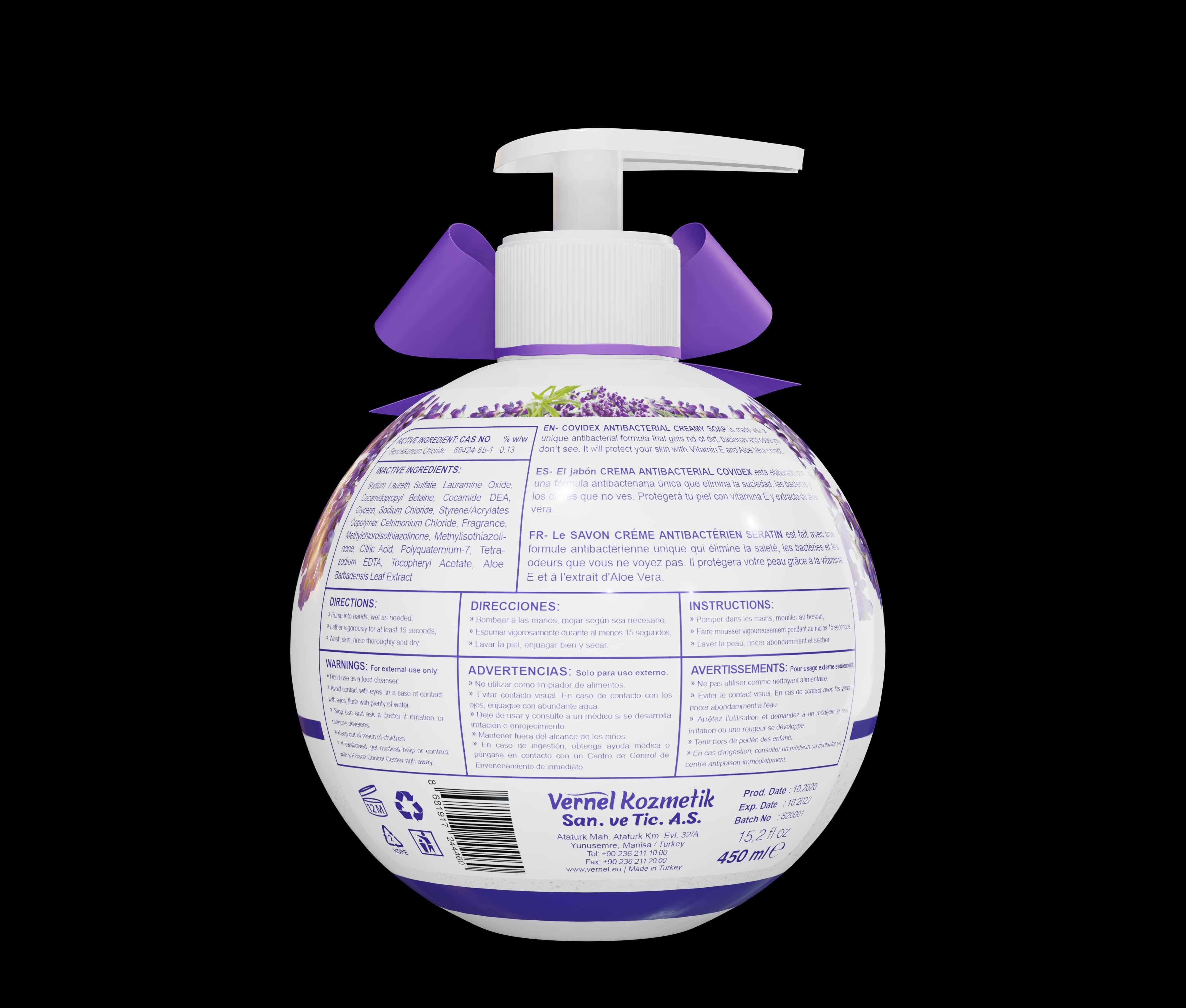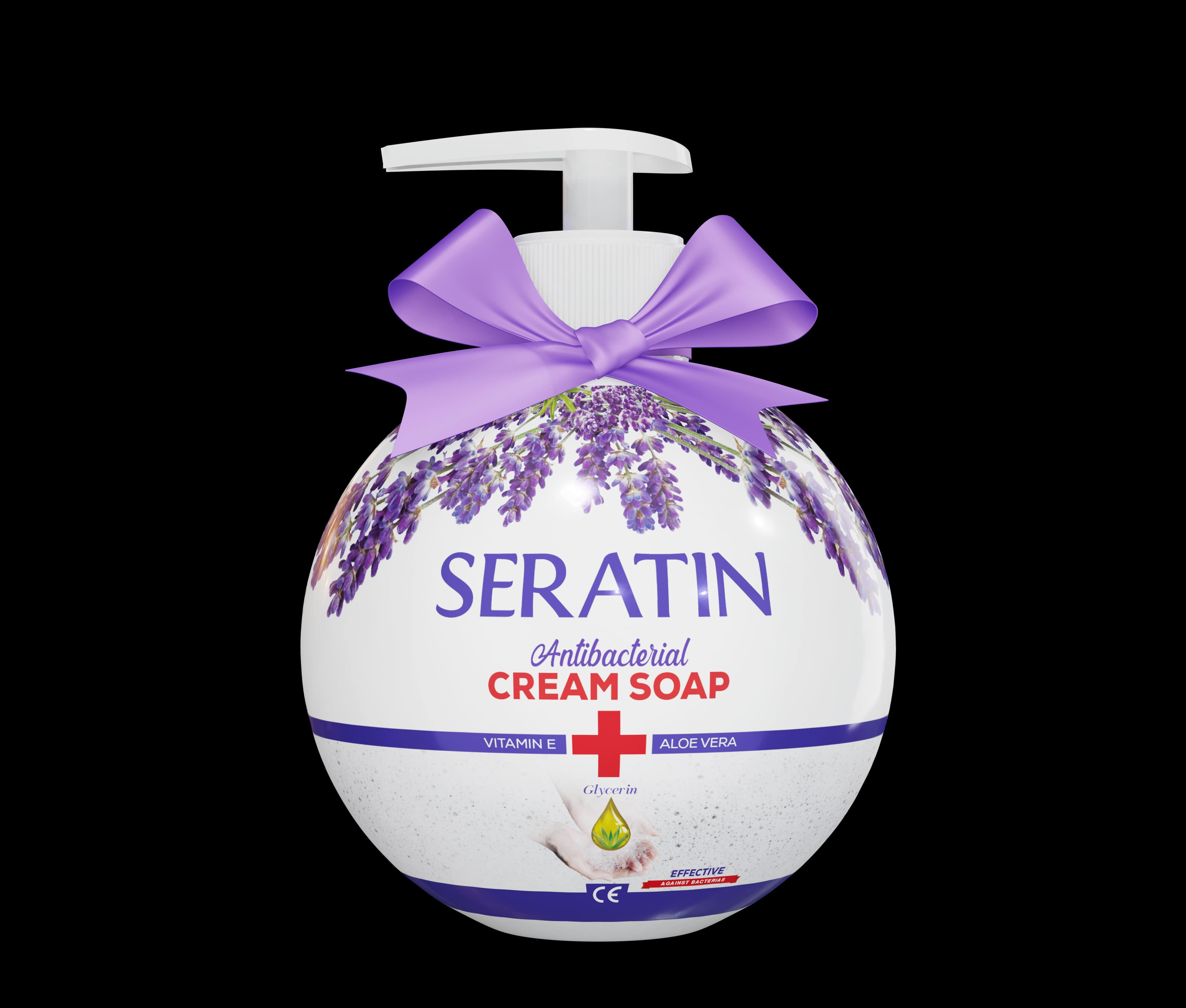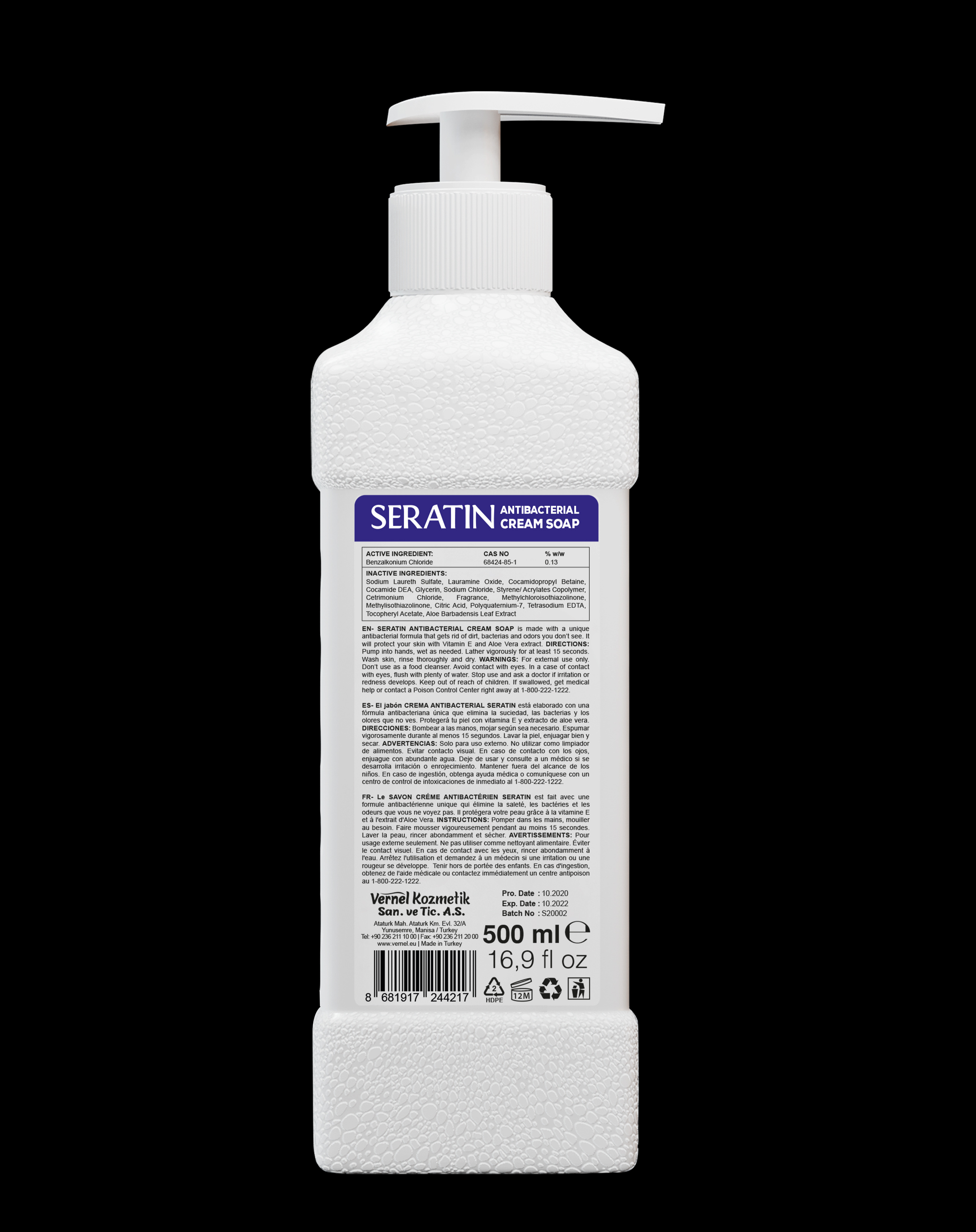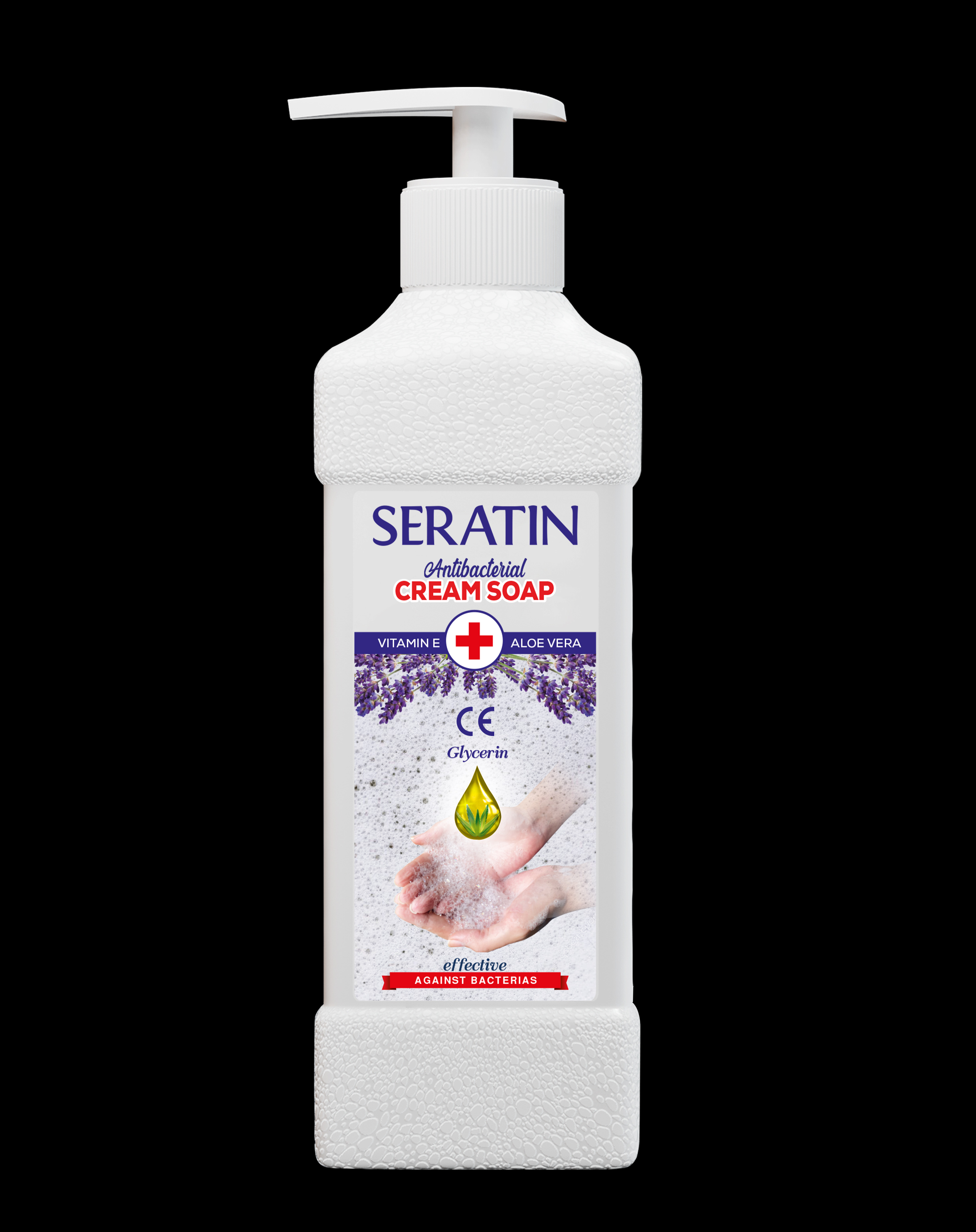 DRUG LABEL: SERATIN
NDC: 79652-011 | Form: SOAP
Manufacturer: VERNEL KOZMETIK SANAYI VE TICARET ANONIM SIRKETI
Category: otc | Type: HUMAN OTC DRUG LABEL
Date: 20201101

ACTIVE INGREDIENTS: BENZALKONIUM CHLORIDE 0.13 g/100 mL
INACTIVE INGREDIENTS: EDETATE SODIUM 0.05 mL/100 mL; CITRIC ACID MONOHYDRATE 0.1 mL/100 mL; ALOE VERA LEAF 0.01 mL/100 mL; FRAGRANCE LAVENDER & CHIA F-153480 0.5 mL/100 mL; .ALPHA.-TOCOPHEROL ACETATE 0.01 mL/100 mL; GLYCERIN 2 mL/100 mL; STYRENE/ACRYLAMIDE COPOLYMER (MW 500000) 0.6 mL/100 mL; COCAMIDOPROPYL BETAINE 3 mL/100 mL; WATER 74.9 mL/100 mL; SODIUM CHLORIDE 1 mL/100 mL; METHYLCHLOROISOTHIAZOLINONE 0.1 mL/100 mL; CETRIMONIUM CHLORIDE 0.5 mL/100 mL; SODIUM LAURETH SULFATE 12 mL/100 mL; COCAMIDE 2 mL/100 mL; LAURAMINE OXIDE 3 mL/100 mL; POLYQUATERNIUM-7 (70/30 ACRYLAMIDE/DADMAC; 1600 KD) 0.1 mL/100 mL

WHEN USING

Benzalkonium chloride 0.13 %

PURPOSE

Antibacterial

WARNINGS

For external use only ; only hands

ACTIVE INGREDIENT

avoid contact with eyes.If contact occurs , rinse eyes thoroughly with water
antimicrobial

STOP USE

- irritation or redness develops
- condition persists for more than 72 hours

KEEP OUT OF REACH OF CHILDREN

If swallowed, get medical help or contact a Poison Control Center right away

INACTIVE INGREDIENT

glycerin, sodium laureth sulfate, lauramine oxide, cocamidopropyl betaine, edetate sodium, water, citric acid monohydrate, polyquaternium-7,aloe vera leaf,cocamide, cetrimonium chloride,methylchloroisothiazolinone,styrene/ acrylamide copolymer, fragrance lavender& chia F-153480, alpha-tocopherol acetate, sodium chloride